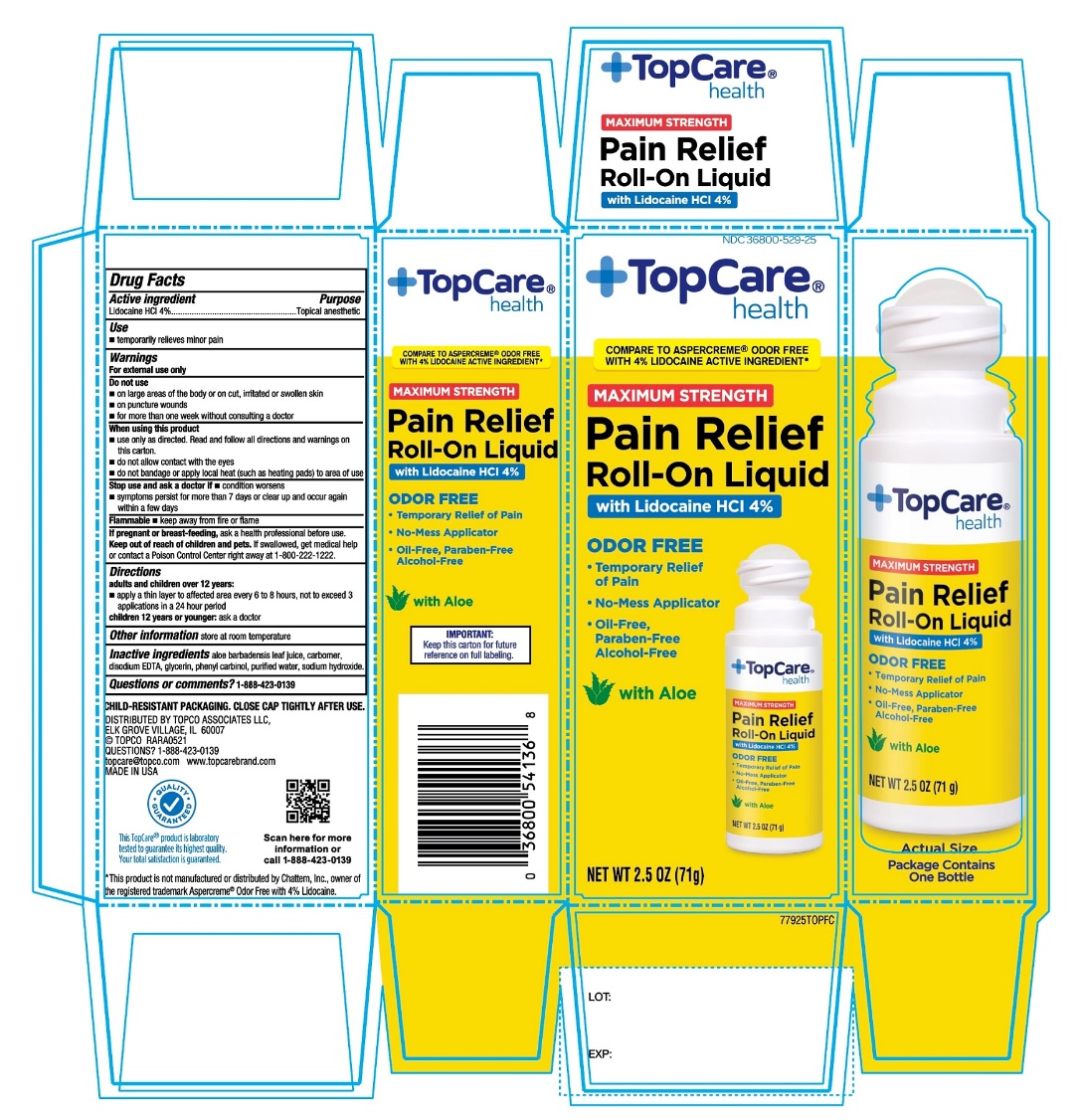 DRUG LABEL: TopCare Pain Relief

NDC: 36800-529 | Form: LIQUID
Manufacturer: TOPCO ASSOCIATES
Category: otc | Type: HUMAN OTC DRUG LABEL
Date: 20251111

ACTIVE INGREDIENTS: LIDOCAINE HYDROCHLORIDE 4 g/100 g
INACTIVE INGREDIENTS: ALOE VERA LEAF; CARBOMER COPOLYMER TYPE B (ALLYL PENTAERYTHRITOL CROSSLINKED); EDETATE DISODIUM; GLYCERIN; BENZYL ALCOHOL; SODIUM HYDROXIDE; WATER

TopCare Max Strength Lidocaine Pain Relieving Liquid

Active ingredient

Lidocaine HCI 4%

Purpose

Topical anesthetic

Uses

- temporarily relieves minor pain

Warnings

For external use only

Do not use

- on large areas of the body or on cut, irritated or swollen skin
- on puncture wounds
- for more than one week without consulting a doctor

When using this product

- use only as directed. Read and follow all directions and warnings on this carton.
- do not allow contact with the eyes
- do not bandage or apply local heat (such as heating pads) to the area of use

Stop use and ask a doctor if

- condition worsens
- symptoms persist for more than 7 days or clear up and occur again within a few days

Flammable

- Keep away from fire or flame

If pregnant or breast-feeding,

ask a health professional before use.

Keep out of reach of children and pets.

If swallowed, get medical help or contact a Poison Control Center right away at 1-800-222-1222.

Directions

adults and children over 12 years:

- apply a thin layer to affected area every 6 to 8 hours, not to exceed 3 applications in a 24 hour period

children 12 years and younger: ask a doctor

Other Information

Store at room temperature

Inactive ingredients

aloe barbadensis leaf juice. Carbomer, disodium EDTA, glycerin, phenyl carbinol, purified water, sodium hydroxide.

Questions or comments?

1-866-467-2748

QUALITY GUARANTEED

This TopCare® product is laboratory tested to guarantee its highest quality.

Your total satisfaction is guaranteed.

PRINCIPAL DISPLAY PANEL

NDC# 36800-529-25

+TopCare health™

COMPARE TO THE ACTIVE INGREDIENT IN ASPERCREME® ODOR FREE WITH 4 % LIDOCAINE*

MAXIMUM STRENGTH

PAIN RELIEF Roll-On Liquid

Lidocaine HCl 4%

ODOR FREE

- Temporary relief of pain
- Helps pain-affected areas
- No-touch applicator
- Oil-Free
- Paraben-Free
- Alcohol-Free

With Aloe

NET WT 2.5 OZ (71 g)

CHILD-RESISTANT PACKAGING. CLOSE CAP TIGHTLY AFTER USE.

DISTRIBUTED BY

TOPCO ASSOCIATES LLC

ELK GROVE VILLAGE, IL 6007

© TOPCO RARA0819

QUESTIONS? 1-888-423-0139

topcare@topco.com

www.topcarebrand.com

*This product is not manufactured or distributed by Chattem, Inc., owner of the registered trademark Aspercreme® Odor Free with 4% Lidocaine.